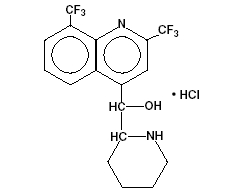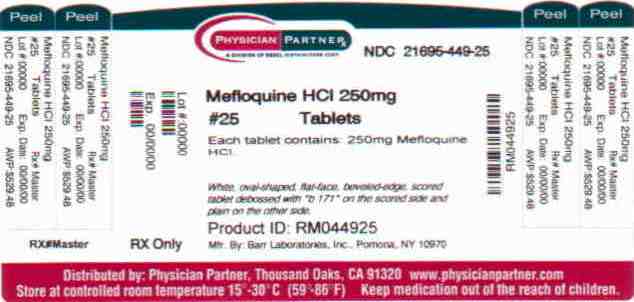 DRUG LABEL: Mefloquine Hydrochloride
NDC: 21695-449 | Form: TABLET
Manufacturer: Rebel Distributors Corp
Category: prescription | Type: HUMAN PRESCRIPTION DRUG LABEL
Date: 20101228

ACTIVE INGREDIENTS: mefloquine hydrochloride 250 mg/1 1
INACTIVE INGREDIENTS: SILICON DIOXIDE; STARCH, CORN; CROSPOVIDONE; LACTOSE MONOHYDRATE; magnesium stearate; CELLULOSE, MICROCRYSTALLINE; STARCH, CORN; POLOXAMER 124; talc

MEFLOQUINE HYDROCHLORIDE TABLETS

1001710105

Rx only

Description:

Mefloquine hydrochloride is an antimalarial agent available as 250-mg tablets of mefloquine hydrochloride (equivalent to 228.0 mg of the free base) for oral administration.

Mefloquine hydrochloride is a 4-quinolinemethanol derivative with the specific chemical name of (R*, S*)-(±)-(α)-2-piperidinyl-2,8-bis (trifluoromethyl)-4-quinolinemethanol hydrochloride. It is a 2-aryl substituted chemical structural analog of quinine. The drug is a white to almost white crystalline compound, slightly soluble in water.

C17H16F6N2O.HCl Molecular Weight: 414.78

The inactive ingredients are colloidal silicon dioxide, corn starch, crospovidone, lactose monohydrate, magnesium stearate, microcrystalline cellulose, pregelatinized starch, poloxamer and talc.

Clinical Pharmacology:

Pharmacokinetics:

Absorption:

The absolute oral bioavailability of mefloquine has not been determined since an intravenous formulation is not available. The bioavailability of the tablet formation compared with an oral solution was over 85%. The presence of food significantly enhances the rate and extent of absorption, leading to about a 40% increase in bioavailability. In healthy volunteers, plasma concentrations peak 6 to 24 hours (median, about 17 hours) after a single dose of mefloquine. In a similar group of volunteers, maximum plasma concentrations in µg/L are roughly equivalent to the dose in milligrams (for example, a single 1000 mg dose produces a maximum concentration of about 1000 µg/L). In healthy volunteers, a dose of 250 mg once weekly, produces maximum steady-state plasma concentrations of 1000 to 2000 µg/L, which are reached after 7 to 10 weeks.

Distribution:

In healthy adults, the apparent volume of distribution is approximately 20 L/kg, indicating extensive tissue distribution. Mefloquine may accumulate in parasitized erythrocytes. Experiments conducted in vitro with human blood using concentrations between 50 and 1000 mg/mL showed a relatively constant erythrocyte-to-plasma concentration ratio of about 2 to 1. The equilibrium reached in less than 30 minutes, was found to be reversible. Protein binding is about 98%. Mefloquine crosses the placenta. Excretion into breast milk appears to be minimal (see PRECAUTIONS: Nursing Mothers).

Metabolism:

Two metabolites have been identified in humans. The main metabolite, 2,8-bis-trifluoromethyl-4-quinoline carboxylic acid, is inactive in Plasmodium falciparum. In a study in healthy volunteers, the carboxylic acid metabolite appeared in plasma 2 to 4 hours after a single oral dose. Maximum plasma concentrations, which were about 50% higher than those of mefloquine, were reached after 2 weeks. Thereafter, plasma levels of the main metabolite and mefloquine declined at a similar rate. The area under the plasma concentration-time curve (AUC) of the main metabolite was 3 to 5 times larger than that of the parent drug. The other metabolite, an alcohol, was present in minute quantities only.

Elimination:

In several studies in healthy adults, the mean elimination half-life of mefloquine varied between 2 and 4 weeks, with an average of about 3 weeks. Total clearance, which is essentially hepatic, is in the order of 30 mL/min. There is evidence that mefloquine is excreted mainly in the bile and feces. In volunteers, urinary excretion of unchanged mefloquine and its main metabolite under steady-state condition accounted for about 9% and 4% of the dose, respectively. Concentrations of other metabolites could not be measured in the urine.

Pharmacokinetics in Special Clinical Situations:

Children and the Elderly:

No relevant age-related changes have been observed in the pharmacokinetics of mefloquine. Therefore, the dosage for children has been extrapolated from the recommended adult dose.

No pharmacokinetic studies have been performed in patients with renal insufficiency since only a small proportion of the drug is eliminated renally. Mefloquine and its main metabolite are not appreciably removed by hemodialysis. No special chemoprophylactic dosage adjustments are indicated for dialysis patients to achieve concentrations in plasma similar to those in healthy persons.

Although clearance of mefloquine may increase in late pregnancy, in general, pregnancy has no clinically relevant effect on the pharmacokinetics of mefloquine.

The pharmacokinetics of mefloquine may be altered in acute malaria.

Pharmacokinetic differences have been observed between various ethnic populations. In practice, however, these are of minor importance compared with host immune status and sensitivity of the parasite.

During long-term prophylaxis (>2 years), the trough concentrations and the elimination half-life of mefloquine were similar to those obtained in the same population after 6 months of drug use, which is when they reached steady state.

In vitro and in vivo studies showed no hemolysis associated with glucose-6-phosphate dehydrogenase deficiency (see ANIMAL TOXICOLOGY).

Microbiology:

Mechanism of Action:

Mefloquine is an antimalarial agent which acts as a blood schizonticide. Its exact mechanism of action is not known.

Activity in Vitro and In Vivo:

Mefloquine is active against the erythrocytic stages of Plasmodium species (see INDICATIONS AND USAGE). However, the drug has no effect against the exoerythrocytic (hepatic) stages of the parasite. Mefloquine is effective against malaria parasites resistant to chloroquine (see INDICATIONS AND USAGE).

Drug Resistance:

Strains of P. falciparum with decreased susceptibility to mefloquine can be selected in vitro or in vivo. Resistance of P. falciparum to mefloquine has been reported, in areas of multi-drug resistance in South East Asia. Increased incidences of resistance have also been reported in other parts of the world.

Cross Resistance:

Cross-resistance between mefloquine and halofantrine and cross-resistance between mefloquine and quinine have been observed in some regions.

Indications and Usage:

Treatment of Acute Malaria Infections:

Mefloquine hydrochloride tablets are indicated for the treatment of mild to moderate acute malaria caused by mefloquine-susceptible strains of P. falciparum (both chloroquine-susceptible and resistant strains) or by Plasmodium vivax. There are insufficient clinical data to document the effect of mefloquine in malaria caused by P. ovale or P. malariae.

Note: Patients with acute P. vivax malaria, treated with mefloquine, are at high risk of relapse because mefloquine does not eliminate exoerythrocytic (hepatic phase) parasites. To avoid relapse, after initial treatment of the acute infection with mefloquine, patients should subsequently be treated with an 8-aminoquinoline (e.g., primaquine).

Prevention of Malaria:

Mefloquine hydrochloride tablets are indicated for the prophylaxis of P. falciparum and P. vivax malaria infections, including prophylaxis of chloroquine-resistant strains of P. falciparum.

Contraindications:

Use of mefloquine hydrochloride tablets are contraindicated in patients with a known hypersensitivity to mefloquine or related compounds (e.g., quinine and quinidine) or to any of the excipients contained in the formulation. Mefloquine hydrochloride tablets should not be prescribed for prophylaxis in patients with active depression, a recent history of depression, generalized anxiety disorder, psychosis, or schizophrenia or other major psychiatric disorders, or with a history of convulsions.

Warnings:

In case of life-threatening, serious or overwhelming malaria infections due to P. falciparum, patients should be treated with an intravenous antimalarial drug. Following completion of intravenous treatment, mefloquine may be given to completethe course of therapy.

Data on the use of halofantrine subsequent to administration of mefloquine suggesta significant, potentially fatal prolongation of the QTc interval of the ECG. Therefore, halofantrine must not be given simultaneously with or subsequent tomefloquine. No data are available on the use of mefloquine after halofantrine (see PRECAUTIONS: Drug Interactions).

Mefloquine may cause psychiatric symptoms in a number of patients, rangingfrom anxiety, paranoia, and depression to hallucinations and psychotic behavior. On occasions, these symptoms have been reported to continue long after mefloquinehas been stopped. Rare cases of suicidal ideation and suicide have beenreported though no relationship to drug administration has been confirmed. Tominimize the chances of these adverse events, mefloquine should not be takenfor prophylaxis in patients with active depression or with a recent history ofdepression, generalized anxiety disorder, psychosis, or schizophrenia or othermajor psychiatric disorders. Mefloquine should be used with caution in patientswith a previous history of depression.

During prophylactic use, if psychiatric symptoms such as acute anxiety, depression, restlessness or confusion occur, these may be considered prodromal to amore serious event. In these cases, the drug must be discontinued and an alternativemedication should be substituted.

Concomitant administration of mefloquine and quinine or quinidine may produceelectrocardiographic abnormalities.

Concomitant administration of mefloquine and quinine or chloroquine may increase the risk of convulsions.

Precautions:

General:

Hypersensitivity reactions ranging from mild cutaneous events to anaphylaxis cannot be predicted.

In patients with epilepsy, mefloquine may increase the risk of convulsions. The drug should therefore be prescribed only for curative treatment in such patients and only if there are compelling medical reasons for its use (see PRECAUTIONS: Drug Interactions).

Caution should be exercised with regard to activities requiring alertness and fine motor coordination such as driving, piloting aircraft, operating machinery and deep-sea diving, as dizziness, a loss of balance, or other disorders of the central or peripheral nervous system have been reported during and following the use of mefloquine. These effects may occur after therapy is discontinued due to the long half-life of the drug. Mefloquine should be used with caution in patients with psychiatric disturbances because mefloquine use has been associated with emotional disturbances (see ADVERSE REACTIONS).

In patients with impaired liver function the elimination of mefloquine may be prolonged, leading to higher plasma levels.

This drug has been administered for longer than 1 year. If the drug is to be administered for a prolonged period, periodic evaluations including liver function tests should be performed. Although retinal abnormalities seen in humans with long-term chloroquine use have not been observed with mefloquine use, long-term feeding of mefloquine to rats resulted in dose-related ocular lesions (retinal degeneration, retinal edema and lenticular opacity at 12.5 mg/kg/day and higher) (see ANIMAL TOXICOLOGY). Therefore, periodic ophthalmic examinations are recommended.

Parenteral studies in animals show that mefloquine, a myocardial depressant, possesses 20% of the antifibrillatory action of quinidine and produces 50% of the increase in the PR interval reported with quinine. The effect of mefloquine on the compromised cardiovascular system has not been evaluated. However, transitory and clinically silent ECG alterations have been reported during the use of mefloquine. Alterations included sinus bradycardia, sinus arrhythmia, first degree AV-block, prolongation of the QTc interval and abnormal T waves (see also cardiovascular effects under PRECAUTIONS: Drug Interactions and ADVERSE REACTIONS). The benefits of mefloquine therapy should be weighed against the possibility of adverse effects in patients with cardiac disease.

Laboratory Tests:

Periodic evaluation of hepatic function should be performed during prolonged prophylaxis.

Information for Patients:

Medication Guide: As required by law, a Mefloquine Hydrochloride Tablets Medication Guide is supplied to patients when mefloquine is dispensed. Patients should be instructed to read the MedGuide when mefloquine is received. The complete text of the MedGuide is reprinted at the end of this document.

Patients should be advised:

- that malaria can be a life-threatening infection in the traveler;
- that mefloquine hydrochloride tablets are being prescribed to help prevent or treat this serious infection;
- that in a small percentage of cases, patients are unable to take this medication because of side effects, and it may be necessary to change medications;
- that when used as prophylaxis, the first dose of mefloquine hydrochloride tablets should be taken 1 week prior to arrival in an endemic area;
- that if the patients experience psychiatric symptoms such as acute anxiety, depression, restlessness or confusion, these may be considered prodromal to a more serious event. In these cases, the drug must be discontinued and an alternative medication should be substituted;
- that no chemoprophylactic regimen is 100% effective, and protective clothing, insect repellents, and bed nets are important components of malaria prophylaxis;
- to seek medical attention for any febrile illness that occurs after return from a malarious area and to inform their physician that they may have been exposed to malaria.

Drug Interactions:

Drug-drug interactions with mefloquine have not been explored in detail. There is one report of cardiopulmonary arrest, with full recovery, in a patient who was taking a beta blocker (propranolol) (see PRECAUTIONS: General). The effects of mefloquine on the compromised cardiovascular system have not been evaluated. The benefits of mefloquine therapy should be weighed against the possibility of adverse effects in patients with cardiac disease.

Because of the danger of a potentially fatal prolongation of the QTc interval, halofantrine must not be given simultaneously with or subsequent to mefloquine (see WARNINGS).

Concomitant administration of mefloquine and other related compounds (e.g., quinine, quinidine and chloroquine) may produce electrocardiographic abnormalities and increase the risk of convulsions (see WARNINGS). If these drugs are to be used in the initial treatment of severe malaria, mefloquine administration should be delayed at least 12 hours after the last dose. There is evidence that the use of halofantrine after mefloquine causes a significant lengthening of the QTc interval. Clinically significant QTc prolongation has not been found with mefloquine alone.

This appears to be the only clinically relevant interaction of this kind with mefloquine, although theoretically, coadministration of other drugs known to alter cardiac conduction (e.g., anti-arrhythmic or beta-adrenergic blocking agents, calcium channel blockers, antihistamines or H1-blocking agents, tricyclic antidepressants and phenothiazines) might also contribute to a prolongation of the QTc interval. There are no data that conclusively establish whether the concomitant administration of mefloquine and the above listed agents has an effect on cardiac function.

In patients taking an anticonvulsant (e.g., valproic acid, carbamazepine, phenobarbital or phenytoin), the concomitant use of mefloquine may reduce seizure control by lowering the plasma levels of the anticonvulsant. Therefore, patients concurrently taking antiseizure medication and mefloquine should have the blood level of their antiseizure medication monitored and the dosage adjusted appropriately (see PRECAUTIONS: General).

When mefloquine is taken concurrently with oral live typhoid vaccines, attenuation of immunization cannot be excluded. Vaccinations with attenuated live bacteria should therefore be completed at least 3 days before the first dose of mefloquine.

No other drug interactions are known. Nevertheless, the effects of mefloquine on travelers receiving comedication, particularly diabetics or patients using anticoagulants, should be checked before departure.

In clinical trials, the concomitant administration of sulfadoxine and pyrimethamine did not alter the adverse reaction profile.

Carcinogenesis, Mutagenesis, Impairment of Fertility:

Carcinogenesis:

The carcinogenic potential of mefloquine was studied in rats and mice in 2-year feeding studies at doses of up to 30 mg/kg/day. No treatment-related increases in tumors of any type were noted.

Mutagenesis:

The mutagenic potential of mefloquine was studied in a variety of assay systems including: Ames test, a host-mediated assay in mice, fluctuation tests and a mouse micronucleus assay. Several of these assays were performed with and without prior metabolic activation. In no instance was evidence obtained for the mutagenicity of mefloquine.

Impairment of Fertility:

Fertility studies in rats at doses of 5, 20, and 50 mg/kg/day of mefloquine have demonstrated adverse effects on fertility in the male at the high dose of 50 mg/kg/day, and in the female at doses of 20 and 50 mg/kg/day. Histopathological lesions were noted in the epididymides from male rats at doses of 20 and 50 mg/kg/day. Administration of 250 mg/week of mefloquine (base) in adult males for 22 weeks failed to reveal any deleterious effects on human spermatozoa.

Pregnancy:

Teratogenic Effects:

Pregnancy Category C: Mefloquine has been demonstrated to be teratogenic in rats and mice at a dose of 100 mg/kg/day. In rabbits, a high dose of 160 mg/kg/day was embryotoxic and teratogenic, and a dose of 80 mg/kg/day was teratogenic but not embryotoxic. There are no adequate and well-controlled studies in pregnant women. However, clinical experience with mefloquine has not revealed an embryotoxic or teratogenic effect. Mefloquine should be used during pregnancy only if the potential benefit justifies the potential risk to the fetus. Women of childbearing potential who are traveling to areas where malaria is endemic should be warned against becoming pregnant. Women of childbearing potential should also be advised to practice contraception during malaria prophylaxis with mefloquine and for up to 3 months thereafter. However, in the case of unplanned pregnancy, malaria chemoprophylaxis with mefloquine is not considered an indication for pregnancy termination.

Nursing Mothers:

Mefloquine is excreted in human milk in small amounts, the activity of which is unknown. Based on a study in a few subjects, low concentrations (3% to 4%) of mefloquine were excreted in human milk following a dose equivalent to 250 mg of the free base. Because of the potential for serious adverse reactions in nursing infants from mefloquine, a decision should be made whether to discontinue the drug, taking into account the importance of the drug to the mother.

Pediatric Use:

Use of mefloquine to treat acute, uncomplicated P. falciparum malaria in pediatric patients is supported by evidence from adequate and well-controlled studies of mefloquine in adults with additional data from published open-label and comparative trials using mefloquine to treat malaria caused by P. falciparum in patients younger than 16 years of age. The safety and effectiveness of mefloquine for the treatment of malaria in pediatric patients below the age of 6 months have not been established.

In several studies, the administration of mefloquine for the treatment of malaria was associated with early vomiting in pediatric patients. Early vomiting was cited in some reports as a possible cause of treatment failure. If a second dose is not tolerated, the patient should be monitored closely and alternative malaria treatment considered if improvement is not observed within a reasonable period of time (see DOSAGE AND ADMINISTRATION).

Geriatric Use:

Clinical studies of mefloquine did not include sufficient numbers of subjects aged 65 and over to determine whether they respond differently from younger subjects. Other reported clinical experience has not identified differences in responses between the elderly and younger patients. Since electrocardiographic abnormalities have been observed in individuals treated with mefloquine (see PRECAUTIONS) and underlying cardiac disease is more prevalent in elderly than in younger patients, the benefits of mefloquine therapy should be weighed against the possibility of adverse cardiac effects in elderly patients.

Adverse Reactions:

Clinical:

At the doses used for treatment of acute malaria infections, the symptoms possibly attributable to drug administration cannot be distinguished from those symptoms usually attributable to the disease itself.

Among subjects who received mefloquine for prophylaxis of malaria, the most frequently observed adverse experience was vomiting (3%). Dizziness, syncope, extrasystoles and other complaints affecting less than 1% were also reported.

Among subjects who received mefloquine for treatment, the most frequently observed adverse experiences included: dizziness, myalgia, nausea, fever, headache, vomiting, chills, diarrhea, skin rash, abdominal pain, fatigue, loss of appetite, and tinnitus. Those side effects occurring in less than 1% included bradycardia, hair loss, emotional problems, pruritus, asthenia, transient emotional disturbances and telogen effluvium (loss of resting hair). Seizures have also been reported.

Two serious adverse reactions were cardiopulmonary arrest in one patient shortly after ingesting a single prophylactic dose of mefloquine while concomitantly using propranolol (see PRECAUTIONS: Drug Interactions), and encephalopathy of unknown etiology during prophylactic mefloquine administration. The relationship of encephalopathy to drug administration could not be clearly established.

Postmarketing:

Postmarketing surveillance indicates that the same kind of adverse experiences are reported during prophylaxis, as well as acute treatment.

The most frequently reported adverse events are nausea, vomiting, loose stools or diarrhea, abdominal pain, dizziness or vertigo, loss of balance, and neuropsychiatric events such as headache, somnolence, and sleep disorders (insomnia, abnormal dreams). These are usually mild and may decrease despite continued use.

Occasionally, more severe neuropsychiatric disorders have been reported such as: sensory and motor neuropathies (including paresthesia, tremor and ataxia), convulsions, agitation or restlessness, anxiety, depression, mood changes, panic attacks, forgetfulness, confusion, hallucinations, aggression, psychotic or paranoid reactions and encephalopathy. Rare cases of suicidal ideation and suicide have been reported though no relationship to drug administration has been confirmed.

Other infrequent adverse events include:

Cardiovascular Disorders:

circulatory disturbances (hypotension, hypertension, flushing, syncope), chest pain, tachycardia or palpitation, bradycardia, irregular pulse, extrasystoles, A-V block, and other transient cardiac conduction alterations.

Skin Disorders:

rash, exanthema, erythema, urticaria, pruritus, edema, hair loss, erythema multiforme, and Stevens-Johnson syndrome.

Musculoskeletal Disorders:

muscle weakness, muscle cramps, myalgia, and arthralgia.

Other Symptoms:

visual disturbances, vestibular disorders including tinnitus and hearing impairment, dyspnea, asthenia, malaise, fatigue, fever, sweating, chills, dyspepsia and loss of appetite.

Laboratory:

The most frequently observed laboratory alterations which could be possibly attributable to drug administration were decreased hematocrit, transient elevation of transaminases, leukopenia and thrombocytopenia. These alterations were observed in patients with acute malaria who received treatment doses of the drug and were attributed to the disease itself.

During prophylactic administration of mefloquine to indigenous populations in malaria-endemic areas, the following occasional alterations in laboratory values were observed: transient elevation of transaminases, leukocytosis or thrombocytopenia.

Because of the long half-life of mefloquine, adverse reactions to mefloquine may occur or persist up to several weeks after the last dose.

Overdosage:

In cases of overdosage with mefloquine, the symptoms mentioned under ADVERSE REACTIONS may be more pronounced. The following procedure is recommended in case of overdosage: Induce vomiting or perform gastric lavage, as appropriate. Monitor cardiac function (if possible by ECG) and neuropsychiatric status for at least 24 hours. Provide symptomatic and intensive supportive treatment as required, particularly for cardiovascular disturbances.

Dosage and Administration (see indications and usage):

Adult Patients:

Treatment of mild to moderate malaria in adults caused by P. vivax or mefloquine-susceptible strains of P. falciparum:

Five tablets (1250 mg) mefloquine hydrochloride to be given as a single oral dose. The drug should not be taken on an empty stomach and should be administered with at least 8 oz (240 mL) of water.

If a full-treatment course with mefloquine does not lead to improvement within 48 to 72 hours, mefloquine hydrochloride tablets should not be used for retreatment. An alternative therapy should be used. Similarly, if previous prophylaxis with mefloquine has failed, mefloquine hydrochloride tablets should not be used for curative treatment.

Note: Patients with acute P. vivax malaria, treated with mefloquine, are at high risk of relapse because mefloquine does not eliminate exoerythrocytic (hepatic phase) parasites. To avoid relapse after initial treatment of the acute infection with mefloquine, patients should subsequently be treated with an 8-aminoquinoline derivative (e.g., primaquine).

Malaria Prophylaxis:

One 250 mg mefloquine hydrochloride tablet once weekly.

Prophylactic drug administration should begin 1 week before arrival in an endemic area. Subsequent weekly doses should be taken regularly, always on the same day of each week, preferably after the main meal. To reduce the risk of malaria after leaving an endemic area, prophylaxis must be continued for 4 additional weeks to ensure suppressive blood levels of the drug when merozoites emerge from the liver. Tablets should not be taken on an empty stomach and should be administered with at least 8 oz (240 mL) of water.

In certain cases, e.g., when a traveler is taking other medication, it may be desirable to start prophylaxis 2 to 3 weeks prior to departure, in order to ensure that the combination of drugs is well tolerated (see PRECAUTIONS: Drug Interactions).

When prophylaxis with mefloquine fails, physicians should carefully evaluate which antimalarial to use for therapy.

Pediatric Patients:

Treatment of mild to moderate malaria in pediatric patients caused by mefloquine-susceptible strains of P. falciparum:

Twenty (20) to 25 mg/kg body weight. Splitting the total therapeutic dose into 2 doses taken 6 to 8 hours apart may reduce the occurrence or severity of adverse effects. Experience with mefloquine hydrochloride tablets in infants less than 3 months old or weighing less than 5 kg is limited. The drug should not be taken on an empty stomach and should be administered with ample water. The tablets may be crushed and suspended in a small amount of water, milk or other beverage for administration to small children and other persons unable to swallow them whole.

If a full-treatment course with mefloquine does not lead to improvement within 48 to 72 hours, mefloquine hydrochloride tablets should not be used for retreatment. An alternative therapy should be used. Similarly, if previous prophylaxis with mefloquine has failed, mefloquine hydrochloride tablets should not be used for curative treatment.

In pediatric patients, the administration of mefloquine hydrochloride tablets for the treatment of malaria has been associated with early vomiting. In some cases, early vomiting has been cited as a possible cause of treatment failure (see PRECAUTIONS). If a significant loss of drug product is observed or suspected because of vomiting, a second full dose of mefloquine hydrochloride tablets should be administered to patients who vomit less than 30 minutes after receiving the drug. If vomiting occurs 30 to 60 minutes after a dose, an additional half-dose should be given. If vomiting recurs, the patient should be monitored closely and alternative malaria treatment considered if improvement is not observed within a reasonable period of time.

The safety and effectiveness of mefloquine hydrochloride tablets to treat malaria in pediatric patients below the age of 6 months have not been established.

Malaria Prophylaxis:

The following doses have been extrapolated from the recommended adult dose. Neither the pharmacokinetics, nor the clinical efficacy of these doses have been determined in children owing to the difficulty of acquiring this information in pediatric subjects. The recommended prophylactic dose of mefloquine hydrochloride tablets is approximately 5 mg/kg body weight once weekly. One 250 mg mefloquine hydrochloride tablet should be taken once weekly in pediatric patients weighing over 45 kg. In pediatric patients weighing less than 45 kg, the weekly dose decreases in proportion to body weight:

30 to 45 kg: 3/4 tablet

20 to 30 kg: 1/2 tablet

10 to 20 kg: 1/4 tablet

5 to 10 kg: 1/8 tablet*

*Approximate tablet fraction based on a dosage of 5 mg/kg body weight. Exact doses for children weighing less than 10 kg may best be prepared and dispensed by pharmacists.

Experience with mefloquine hydrochloride tablets in infants less than 3 months old or weighing less than 5 kg is limited.

How Supplied:

Mefloquine Hydrochloride Tablets are available as:

250 mg: White, oval-shaped, flat-faced, beveled-edge, scored tablet containing 250 mg of mefloquine hydrochloride.

Debossed with stylized B 171 on the scored side and plain on the other side.

Available in bottle of:

7 tablets NDC 21695-449-07

25 tablets NDC 21695-449-25

Store at 20°-25°C (68°-77°F); excursions permitted to 15°-30°C (59°-86°F) [see

USP].

ANIMAL TOXICOLOGY:

Ocular lesions were observed in rats fed mefloquine daily for 2 years. All surviving rats given 30 mg/kg/day had ocular lesions in both eyes characterized by retinal degeneration, opacity of the lens, and retinal edema. Similar but less severe lesions were observed in 80% of female and 22% of male rats fed 12.5 mg/kg/day for 2 years. At doses of 5 mg/kg/day, only corneal lesions were observed. They occurred in 9% of rats studied.

Medication Guide

Mefloquine Hydrochloride Tablets

to Prevent Malaria

This Medication Guide is intended only for travelers who are taking mefloquinehydrochloride tablets (mefloquine) to prevent malaria. The information may not apply to patients who are sick with malaria and who are taking mefloquine to treat malaria.

An information wallet card is provided at the end of this Medication Guide. Cut it out and carry it with you when you are taking mefloquine.

This Medication Guide was revised in September 2003. Please read it before you start taking mefloquine and each time you get a refill. There may be new information. This Medication Guide does not take the place of talking with your prescriber (doctor or other health care provider) about mefloquine and malaria prevention. Only you and your prescriber can decide if mefloquine is right for you. If you cannot take mefloquine, you may be able to take a different medicine to prevent malaria.

What is the most important information I should know about Mefloquine?

1. Take Mefloquine exactly as prescribed to prevent malaria.
  Malaria is an infection that can cause death, and is spread to humans through mosquito bites. If you travel to parts of the world where the mosquitoes carry the malaria parasite, you must take a malaria prevention medicine. Mefloquine is one of a small number of medications approved to prevent and to treat malaria. If taken correctly, mefloquine is effective at preventing malaria but, like all medications, it may produce side effects in some patients.
2. Mefloquine can rarely cause serious mental problems in some patients.
  The most frequently reported side effects with mefloquine, such as nausea, difficulty sleeping, and bad dreams are usually mild and do not cause people to stop taking the medicine. However, people taking mefloquine occasionally experience severe anxiety, feelings that people are against them, hallucinations (seeing or hearing things that are not there, for example), depression, unusual behavior, or feeling disoriented. There have been reports that in some patients these side effects continue after mefloquine is stopped. Some patients taking mefloquine think about killing themselves, and there have been rare reports of suicides. It is not known whether mefloquine was responsible for these suicides.
3. You need to take malaria prevention medicine before you travel to a malariaarea, while you are in a malaria area, and after you return from a malaria area.
  Medicines approved in the United States for malaria prevention include mefloquine, doxycycline, atovaquone/proguanil, hydroxychloroquine, and chloroquine. Not all of these drugs work equally as well in all areas of the world where there is malaria. The chloroquines, for example, do not work in areas where the malaria parasite has developed resistance to chloroquine. Mefloquine may be effective against malaria that is resistant to chloroquine or other drugs. All drugs to treat malaria have side effects that are different for each one. For example, some may make your skin more sensitive to sunlight (mefloquine does not do this). However, if you use mefloquine to prevent malaria and you develop a sudden onset of anxiety, depression, restlessness, confusion (possible signs of more serious mental problems), or you develop other serious side effects, contact a doctor or other healthcare provider. It may be necessary to stop taking mefloquine and use another malaria prevention medicine instead. If you can’t get another medicine, leave the malaria area. However, be aware that leaving the malaria area may not protect you from getting malaria. You still need to take a malaria prevention medicine.

Who should not take Mefloquine?

Do not take mefloquine to prevent malaria if you

- have depression or had depression recently
- have had recent mental illness or problems, including anxiety disorder, schizophrenia (a severe type of mental illness), or psychosis (losing touch with reality)
- have or had seizures (epilepsy or convulsions)
- are allergic to quinine or quinidine (medicines related to mefloquine)

Tell your prescriber about all your medical conditions. Mefloquine may not be right for you if you have certain conditions, especially the ones listed below:

- Heart disease. Mefloquine may not be right for you.
- Pregnancy. Tell your prescriber if you are pregnant or plan to become pregnant. It is dangerous for the mother and for the unborn baby (fetus) to get malaria during pregnancy. Therefore, ask your prescriber if you should take mefloquine or another medicine to prevent malaria while you are pregnant.
- Breast feeding. Mefloquine can pass through your milk and may harm the baby. Therefore, ask your prescriber whether you will need to stop breast feeding or use another medicine.
- Liver problems.

Tell your prescriber about all the medicines you take, including prescription andnon-prescription medicines, vitamins, and herbal supplements. Some medicines may give you a higher chance of having serious side effects from mefloquine.

How should I take Mefloquine?

Take mefloquine exactly as prescribed. If you are an adult or pediatric patientweighing 45 kg (99 pounds) or less, your prescriber will tell you the correct dosebased on your weight.

To prevent malaria

- For adults and pediatric patients weighing over 45 kg, take 1 tablet of mefloquine at least 1 week before you travel to a malaria area (or 2 to 3 weeks before you travel to a malaria area, if instructed by your prescriber). This starts the prevention and also helps you see how mefloquine affects you and the other medicines you take. Take 1 mefloquine tablet once a week, on the same day each week, while in a malaria area.
- Continue taking mefloquine for 4 weeks after returning from a malaria area. If you cannot continue taking mefloquine due to side effects or for other reasons, contact your prescriber.
- Take mefloquine just after a meal and with at least 1 cup (8 ounces) of water.
- For children, mefloquine can be given with water or crushed and mixed with water or sugar water. The prescriber will tell you the correct dose for children based on the child’s weight.
- If you are told by a doctor or other health care provider to stop taking mefloquine due to side effects or for other reasons, it will be necessary to take another malaria medicine. You must take malaria prevention medicine beforeyou travel to a malaria area, while you are in a malaria area, and after youreturn from a malaria area. If you don’t have access to a doctor or otherhealth care provider or to another medicine besides mefloquine and have tostop taking it, leave the malaria area. However, be aware that leaving themalaria area may not protect you from getting malaria. You still need to takea malaria prevention medicine.

What should I avoid while taking Mefloquine?

- Halofantrine (marketed under various brand names), a medicine used to treat malaria. Taking both of these medicines together can cause serious heart problems that can cause death.
- Do not become pregnant. Women should use effective birth control while taking mefloquine.
- Quinine, quinidine, or chloroquine (other medicines used to treat malaria). Taking these medicines with mefloquine could cause changes in your heart rate or increase the risk of seizures.

In addition:

- Be careful driving or in other activitiesneeding alertness and careful movements (fine motor coordination). Mefloquine can cause dizziness or loss of balance, even after you stop taking it.
- Be aware that certain vaccines may not work if given while you are taking Mefloquine. Your prescriber may want you to finish taking your vaccines at least 3 days before starting mefloquine.

What are the possible side effects of Mefloquine?

Mefloquine, like all medicines, may cause side effects in some patients. The most frequently reported side effects with mefloquine when used for prevention of malaria include nausea, vomiting, diarrhea, dizziness, difficulty sleeping, and bad dreams. These are usually mild and do not cause people to stop taking the medicine.

Mefloquine may cause serious mental problems in some patients. (See “What is the most important information I should know about Mefloquine?”).

Mefloquine may affect your liver and your eyes if you take it for a long time. Your prescriber will tell you if you should have your eyes and liver checked while taking mefloquine.

What else should I know about preventing malaria?

- Find out whether you need malaria prevention. Before you travel, talk with your prescriber about your travel plans to determine whether you need to take medicine to prevent malaria. Even in those countries where malaria is present, there may be areas of the country that are free of malaria. In general, malaria is more common in rural (country) areas than in big cities, and it is more common during rainy seasons, when mosquitoes are most common. You can get information about the areas of the world where malaria occurs from the Centers for Disease Control and Prevention (CDC) and from local authorities in the countries you visit. If possible, plan your travel to reduce the risk of malaria.
- Take medicine to prevent malaria infection. Without malaria prevention medicine, you have a higher risk of getting malaria. Malaria starts with flu-like symptoms, such as chills, fever, muscle pains, and headaches. However, malaria can make you very sick or cause death if you don’t seek medical help immediately. These symptoms may disappear for a while, and you may think you are well. But, the symptoms return later and then it may be too late for successful treatment.
  Malaria can cause confusion, coma, and seizures. It can cause kidney failure, breathing problems, and severe damage to red blood cells. However, malaria can be easily diagnosed with a blood test, and if caught in time, can be effectively treated
  If you get flu-like symptoms (chills, fever, muscle pains, or headaches) after you return from a malaria area, get medical help right away and tell your prescriber that you may have been exposed to malaria.
  People who have lived for many years in areas with malaria may have some immunity to malaria (they do not get it as easily) and may not take malaria prevention medicine. This does not mean that you don’t need to take malaria
- Protect against mosquito bites. Medicines do not always completely prevent your catching malaria from mosquito bites. So protect yourself very well against mosquitoes. Cover your skin with long sleeves and long pants, and use mosquito repellent and bed nets while in malaria areas. If you are out in the bush, you may want to pre-wash your clothes with permethrin. This is a mosquito repellent that may be effective for weeks after use. Ask your prescriber for other ways to protect yourself.

General information about the safe and effective use of Mefloquine.

Medicines are sometimes prescribed for conditions not listed in Medication Guides. If you have any concerns about mefloquine, ask your prescriber. This Medication Guide contains certain important information for travelers visiting areas with malaria. Your prescriber or pharmacist can give you information about mefloquine that was written for health care professionals. Do not use mefloquine for a condition for which it was not prescribed. Do not share mefloquine with other people.

This Medication Guide has been approved by the U.S. Food and Drug Administration.

MANUFACTURED BY

BARR LABORATORIES, INC.

POMONA, NY 10970

BR-171

Repackaged by:

Rebel Distributors Corp

Thousand Oaks, CA 91320